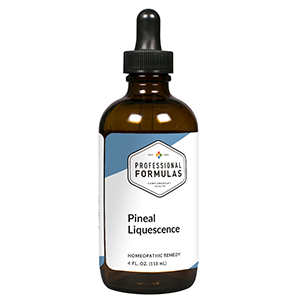 DRUG LABEL: Pineal Liquescence
NDC: 63083-3030 | Form: LIQUID
Manufacturer: Professional Complementary Health Formulas
Category: homeopathic | Type: HUMAN OTC DRUG LABEL
Date: 20190815

ACTIVE INGREDIENTS: ARTEMISIA ANNUA FLOWERING TOP 2 [hp_X]/118 mL; MELATONIN 2 [hp_X]/118 mL; SCUTELLARIA LATERIFLORA WHOLE 2 [hp_X]/118 mL; VALERIAN 2 [hp_X]/118 mL; CENTELLA ASIATICA LEAF 3 [hp_X]/118 mL; STELLARIA MEDIA 3 [hp_X]/118 mL; BOS TAURUS BRAIN 6 [hp_X]/118 mL; CALCIUM 6 [hp_X]/118 mL; MAGNESIUM 6 [hp_X]/118 mL; SUS SCROFA PINEAL GLAND 6 [hp_X]/118 mL; ZINC 6 [hp_X]/118 mL; PHOSPHATIDYL SERINE 12 [hp_X]/118 mL; DOPAMINE 12 [hp_X]/118 mL; SEROTONIN 12 [hp_X]/118 mL
INACTIVE INGREDIENTS: ALCOHOL; WATER

T30

ACTIVE INGREDIENTS

Chamomilla 2X
Melatonin 2X
Scutellaria lateriflora 2X
Valeriana officinalis 2X
Gotu kola 3X
Stellaria media 3X
Brain 6X
Calcium 6X
Magnesium 6X
Pineal 6X
Zinc 6X
Phosphatidylserine 12X
Dopamine 12X, 16X
Serotonin 12X, 16X

QUESTIONS

Professional Formulas

PO Box 2034 Lake Oswego, OR 97035

INDICATIONS

For the temporary relief of fatigue, anxiety, apathy, sadness, excess sleepiness or insomnia, irritability, minor muscle aches or tenderness, or feelings of discomfort or uneasiness.*

PURPOSE

*Claims based on traditional homeopathic practice, not accepted medical evidence. Not FDA evaluated.

WARNINGS

In case of overdose, get medical help or contact a poison control center right away.

Keep out of the reach of children.

PREGNANCY OR BREAST FEEDING

If pregnant or breastfeeding, ask a healthcare professional before use.

DIRECTIONS

Place drops under tongue 30 minutes before/after meals. Adults and children 12 years and over: Take one full dropper up to 2 times per day. Consult a physician for use in children under 12 years of age.

OTHER INFORMATION

Tamper resistant. If seal is broken, do not use. After opening, close container tightly and store at room temperature away from heat.

INACTIVE INGREDIENTS

20% ethanol, purified water.

LABEL

Est 1985

Professional Formulas

Complementary Health

Pineal Liquescence

Homeopathic Remedy

4 FL. OZ. (118 mL)